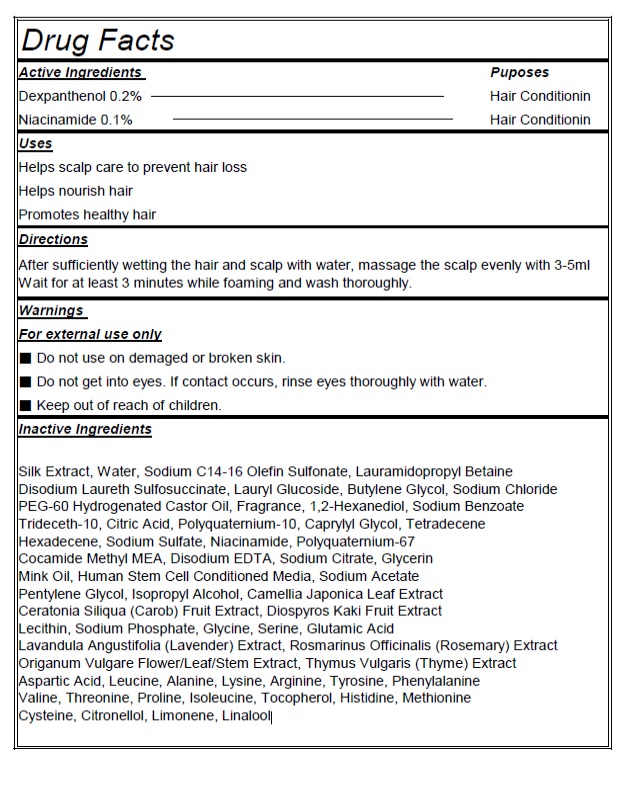 DRUG LABEL: MIRACLE STEMCELL ALL-IN-ONE
NDC: 24765-001 | Form: SHAMPOO
Manufacturer: PHARMACAL-INTERNATIONAL. CO., LTD
Category: otc | Type: HUMAN OTC DRUG LABEL
Date: 20231221

ACTIVE INGREDIENTS: DEXPANTHENOL 0.2 g/100 g; NIACINAMIDE 0.1 g/100 g
INACTIVE INGREDIENTS: OREGANO FLOWERING TOP; WATER; SODIUM C14-16 OLEFIN SULFONATE; LAURAMIDOPROPYL BETAINE; DISODIUM LAURETH SULFOSUCCINATE; LAURYL GLUCOSIDE; BUTYLENE GLYCOL; SODIUM CHLORIDE; PEG-60 HYDROGENATED CASTOR OIL; 1,2-HEXANEDIOL; SODIUM BENZOATE; TRIDECETH-10; CITRIC ACID ACETATE; POLYQUATERNIUM-10 (1000 MPA.S AT 2%); MENTHOL; CAPRYLYL GLYCOL; TETRADECENE (MIXED ISOMERS); HEXADECENE (MIXED ISOMERS); SODIUM SULFATE; POLYQUATERNIUM-68; COCOYL METHYL MONOETHANOLAMINE; EDETATE DISODIUM ANHYDROUS; SODIUM CITRATE, UNSPECIFIED FORM; GLYCERIN; SODIUM ACETATE; PENTYLENE GLYCOL; ISOPROPYL ALCOHOL; CAMELLIA JAPONICA LEAF; CAROB; PERSIMMON; LECITHIN, SOYBEAN; SODIUM PHOSPHATE; GLYCINE; SERINE; GLUTAMIC ACID; LAVANDULA ANGUSTIFOLIA SUBSP. ANGUSTIFOLIA FLOWERING TOP; ROSEMARY; THYME; ASPARTIC ACID; LEUCINE; ALANINE; LYSINE; ARGININE; TYROSINE; PHENYLALANINE; VALINE; THREONINE; PROLINE; ISOLEUCINE; TOCOPHEROL; HISTIDINE; METHIONINE; CYSTEINE; .BETA.-CITRONELLOL, (R)-; LIMONENE, (+)-; LINALOOL, (+/-)-

Actvie Ingrdients Purpose

Dexpanthenol 0.2% Hair Conditionin
Niacinamide 0.1% Hair Conditionin

Indication and Usage

Helps scalp care to prevent hair loss
Helps nourish hair
Promotes healthy hair

Warnings

■ For external use only

■ Do not use on damaged or broken skin

■ Do not get into eyes. If contact occurs, rinse eyes thoroughly with water.

■ Keep out of reach of children

Keep out of reach of children

Directions

After sufficiently wetting the hair and scalp with water, massage the scalp evenly with 3-5mlWait for at least 3 minutes while foaming and wash thoroughly.

Inactive Ingredients

Water, Sodium C14-16 Olefin Sulfonate, Lauramidopropyl Betaine, Disodium Laureth Sulfosuccinate, Lauryl Glucoside, Butylene Glycol, Sodium Chloride, PEG-60 Hydrogenated Castor Oil, Fragrance, 1,2-Hexanediol, Sodium Benzoate, Trideceth-10, Citric Acid, Polyquaternium-10, Menthol, Caprylyl Glycol, Tetradecene, Hexadecene, Sodium Sulfate, Cocamide Methyl MEA, Disodium EDTA, Sodium Citrate, Glycerin, Sodium Acetate, Pentylene Glycol, Isopropyl Alcohol, Camellia Japonica Leaf Extract, Ceratonia Siliqua (Carob) Fruit Extract, Diospyros Kaki Fruit Extract, Lecithin, Sodium Phosphate, Glycine, Serine, Glutamic Acid, Lavandula Angustifolia (Lavender) Extract, Rosmarinus Officinalis (Rosemary) Extract, Origanum Vulgare Flower/Leaf/Stem Extract, Thymus Vulgaris (Thyme) Extract, Aspartic Acid, Leucine, Alanine, Lysine, Arginine, Tyrosine, Phenylalanine, Valine, Threonine, Proline, Isoleucine, Tocopherol, Histidine, Methionine, Cysteine, Citronellol, Limonene, Linalool